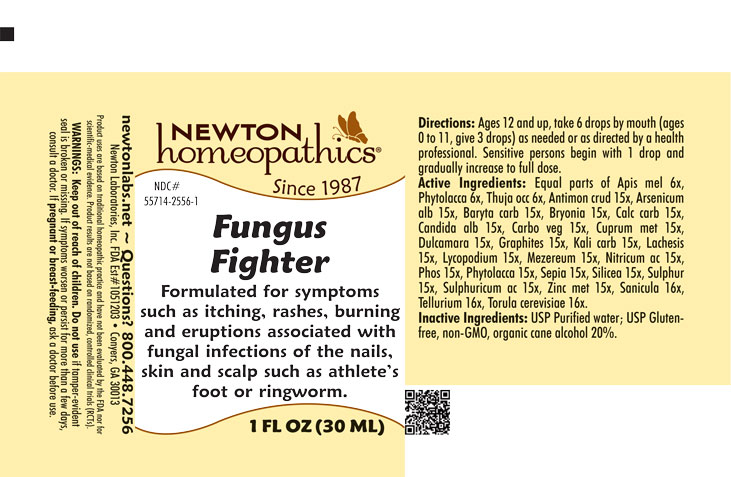 DRUG LABEL: Fungus Fighter
NDC: 55714-2556 | Form: LIQUID
Manufacturer: Newton Laboratories, Inc.
Category: homeopathic | Type: HUMAN OTC DRUG LABEL
Date: 20250819

ACTIVE INGREDIENTS: SILICON DIOXIDE 15 [hp_X]/1 mL; SULFUR 15 [hp_X]/1 mL; SULFURIC ACID 15 [hp_X]/1 mL; ZINC 15 [hp_X]/1 mL; APIS MELLIFERA 6 [hp_X]/1 mL; THUJA OCCIDENTALIS LEAFY TWIG 6 [hp_X]/1 mL; CANDIDA ALBICANS 15 [hp_X]/1 mL; SANICULA EUROPAEA LEAF 16 [hp_X]/1 mL; TELLURIUM 16 [hp_X]/1 mL; SACCHAROMYCES CEREVISIAE 16 [hp_X]/1 mL; ANTIMONY TRISULFIDE 15 [hp_X]/1 mL; ARSENIC TRIOXIDE 15 [hp_X]/1 mL; BARIUM CARBONATE 15 [hp_X]/1 mL; BRYONIA ALBA ROOT 15 [hp_X]/1 mL; OYSTER SHELL CALCIUM CARBONATE, CRUDE 15 [hp_X]/1 mL; ACTIVATED CHARCOAL 15 [hp_X]/1 mL; COPPER 15 [hp_X]/1 mL; SOLANUM DULCAMARA TOP 15 [hp_X]/1 mL; GRAPHITE 15 [hp_X]/1 mL; POTASSIUM CARBONATE 15 [hp_X]/1 mL; LACHESIS MUTA VENOM 15 [hp_X]/1 mL; LYCOPODIUM CLAVATUM SPORE 15 [hp_X]/1 mL; DAPHNE MEZEREUM BARK 15 [hp_X]/1 mL; NITRIC ACID 15 [hp_X]/1 mL; PHOSPHORUS 15 [hp_X]/1 mL; PHYTOLACCA AMERICANA ROOT 15 [hp_X]/1 mL; SEPIA OFFICINALIS JUICE 15 [hp_X]/1 mL
INACTIVE INGREDIENTS: ALCOHOL; WATER

Fungus 2556L

INDICATIONS & USAGE SECTION

Formulated for symptoms such as itching, rashes, burning and eruptions associated with fungal infections of the nails, skin and scalp such as athlete's foot or ringworm.

DOSAGE & ADMINISTRATION SECTION

Directions: Ages 12 and up, take 6 drops by mouth (ages 0 to 11, give 3 drops) as needed or as directed by a health professional. Sensitive persons begin with 1 drop and gradually increase to full dose.

OTC - ACTIVE INGREDIENT SECTION

Equal parts of Apis mel. 6x, Phytolacca 6x, Thuja occ. 6x, Antimon. crud. 15x, Arsenicum alb. 15x, Baryta carb. 15x, Bryonia 15x, Calc. carb.15x, Candida alb. 15x, Carbo veg. 15x, Cuprum met. 15x, Dulcamara 15x, Graphites 15x, Kali carb. 15x, Lachesis 15x, Lycopodium 15x, Mezereum 15x, Nitricum ac. 15x, Phos. 15x, Phytolacca 15x, Sepia 15x, Silicea 15x, Sulphur 15x, Sulphuricum ac. 15x, Zinc. met. 15x, Sanicula 16x, Tellurium 16x, Torula cerevisiae 16x.

OTC - PURPOSE SECTION

Formulated for symptoms such as itching, rashes, burning and eruptions associated with fungal infections of the nails,skin and scalp such as athlete's foot or wingworm.

INACTIVE INGREDIENT SECTION

Inactive Ingredients: USP Purified Water; USP Gluten-free, non-GMO, organic cane alcohol 20%.

QUESTIONS SECTION

newtonlabs.net – Questions? 800.448.7256

Newton Laboratories, Inc. FDA Est # 1051203 - Conyers, GA 30013

WARNINGS SECTION

WARNINGS: Keep out of reach of children. Do not use if tamper-evident seal is broken or missing. If symptoms worsen or persist for more than a few days, consult a doctor. If pregnant or breast-feeding, ask a doctor before use.

OTC - PREGNANCY OR BREAST FEEDING SECTION

If pregnant or breast-feeding, ask a doctor before use.

OTC - KEEP OUT OF REACH OF CHILDREN SECTION

Keep out of reach of children.